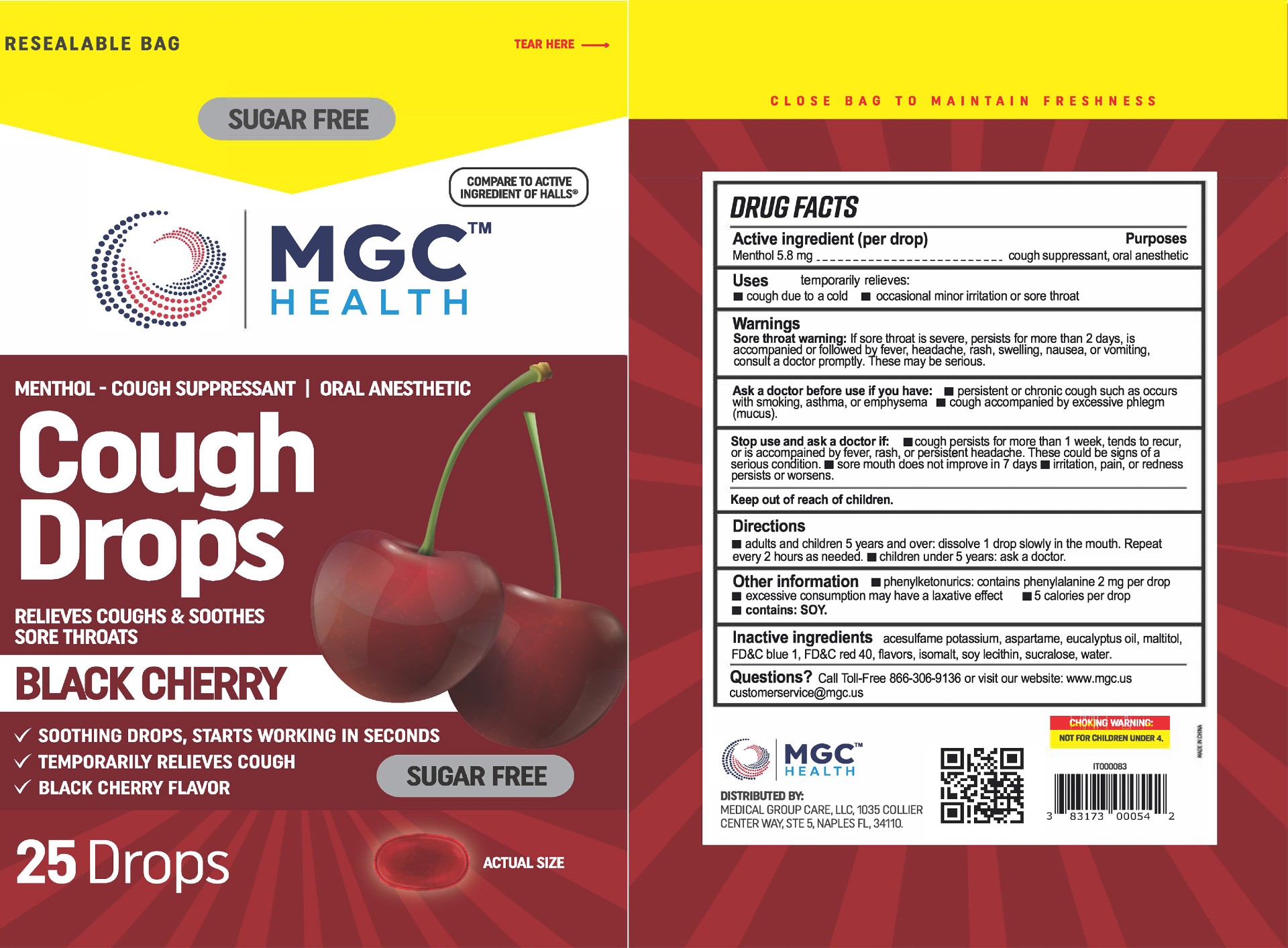 DRUG LABEL: MGC Health
NDC: 83698-127 | Form: LOZENGE
Manufacturer: Xiamen Kang Zhongyuan Biotechnology Co., Ltd.
Category: otc | Type: HUMAN OTC DRUG LABEL
Date: 20251229

ACTIVE INGREDIENTS: MENTHOL 5.8 mg/1 1
INACTIVE INGREDIENTS: ACESULFAME POTASSIUM; EUCALYPTUS OIL; FD&C RED NO. 40; ISOMALT; FD&C BLUE NO. 1; LECITHIN, SOYBEAN; WATER; ASPARTAME

YNBY-MGC BC SF 25-70 2023

Active Ingredient(s)

Menthol 5.8

Purpose

Purposes cough suppressant, oral anesthetic

Use

temporary relieves: ■ cough due to cold ■ occasional minor irritation or sore throat

Warnings

Sore throat warning: If sore throat is severe, persists for more than 2 days, is accompanied or follow headache, rash, swelling, nausea, or vomiting, consult a doctor promptly. These may be serious.

Ask a doctor before use if you have: ■ persistent or chronic cough such as occurs with smoking, asthma, or emphysema ■ cough accompanied by excessive phlegm (mucus).

Stop use and ask a doctor if ■ cough persists for more than 1 week, tends to recur, or is accompained by fever, rash, or persistent headache. These could be signs of a serius condition. ■ sore mouth does not improve in 7 days ■ irritation, pain, or redness persists or worsens.

Keep out of reach of children.

Directions

• adults and children 5 years and over: dissolve 1 drop slowly in the mouth. Repeat every 2 hours as needed.

• children under 5 years: ask a doctor.

Other information

phenylketonurics: contains phenylalanine 2 mg per drop

excessive consumption may have a laxative effect
contains: SOY.

-5 calories per drop

Inactive ingredients

Acesulfame potassium, aspartame, eucalyptus oil, maltitol, FD&C blue 1. FD&C red 40, flavors. isomalt, soy lecithin, sucralose, water.

QUESTIONS

Call Toll-Free 866-306-9136 or visit our website: www.mgc.us

customerservice@mgc.us

Package Label - Principal Display Panel

25 Drops NDC: 61658-127-25